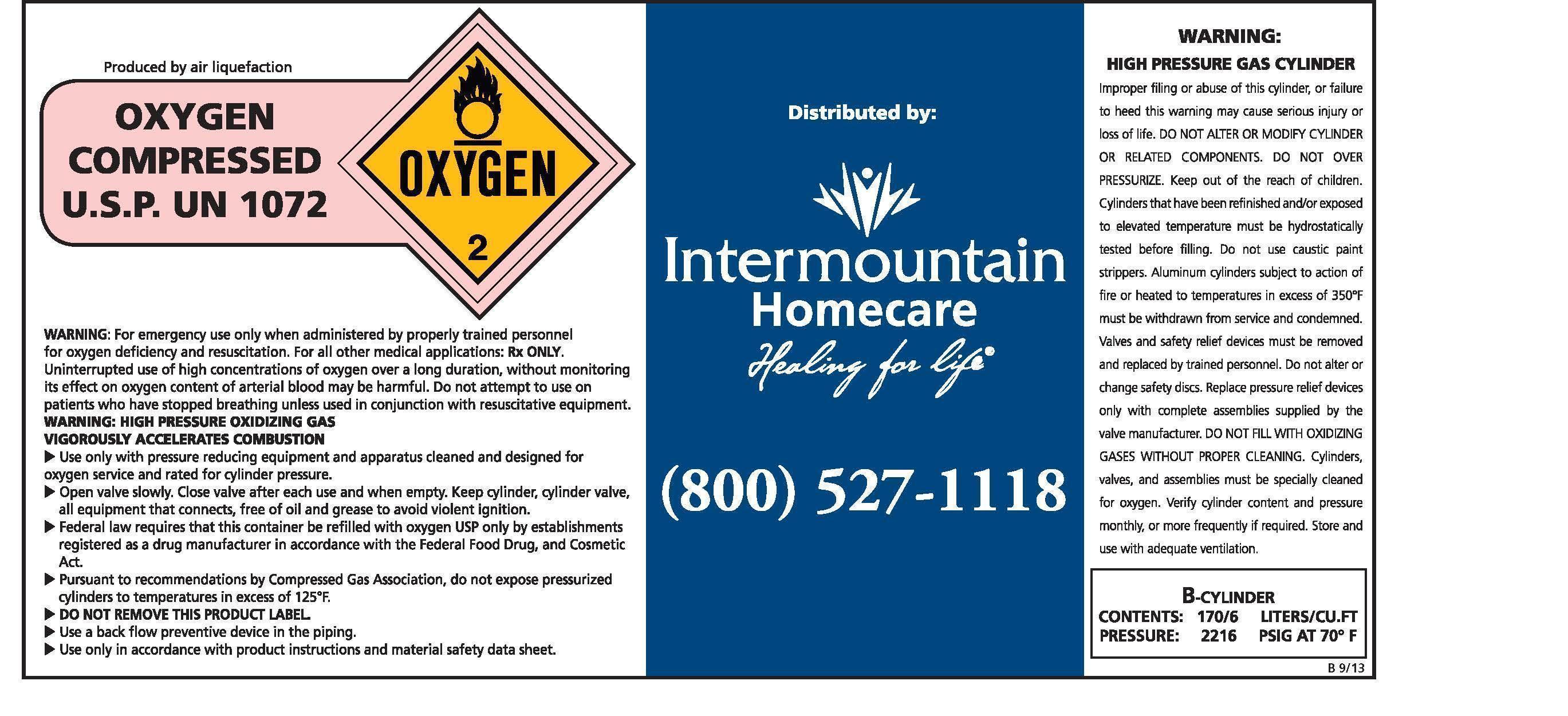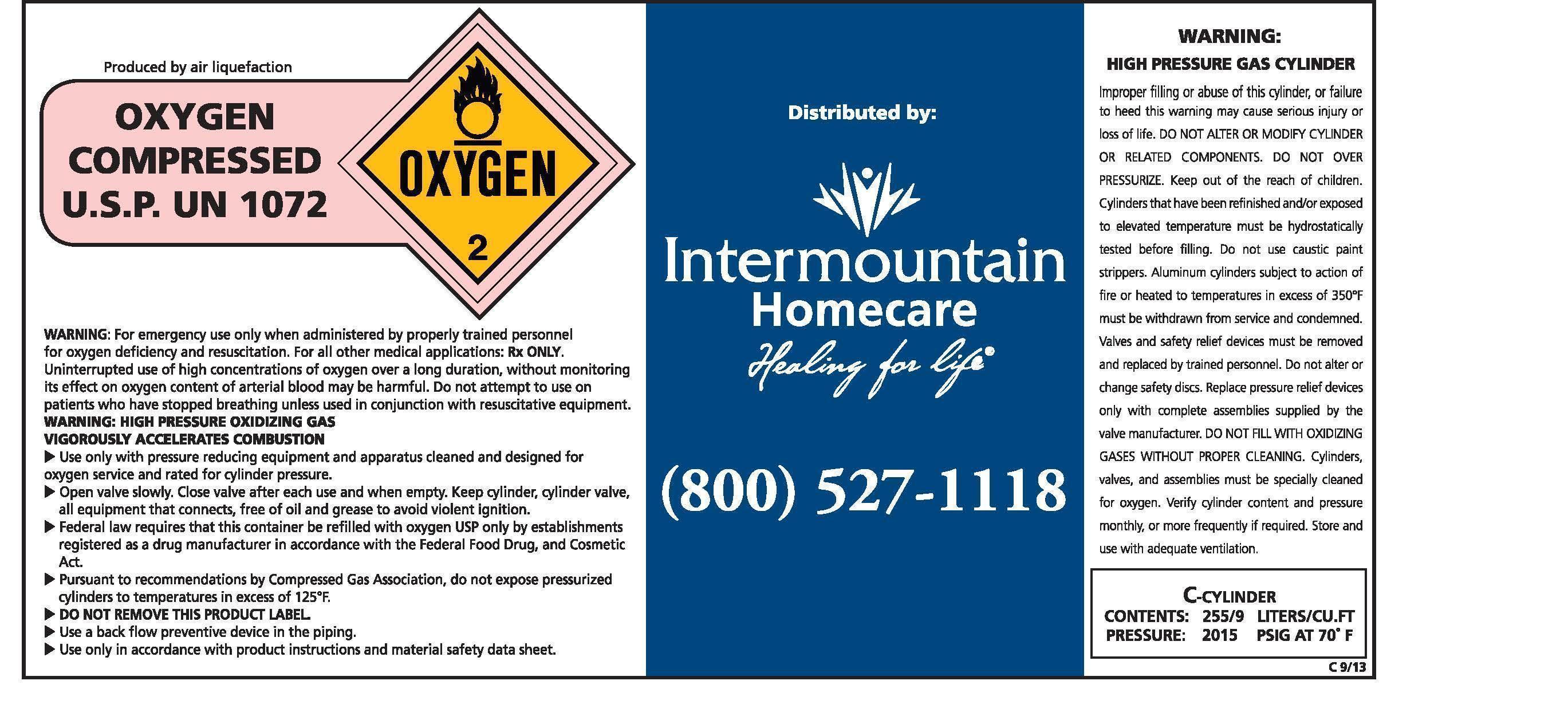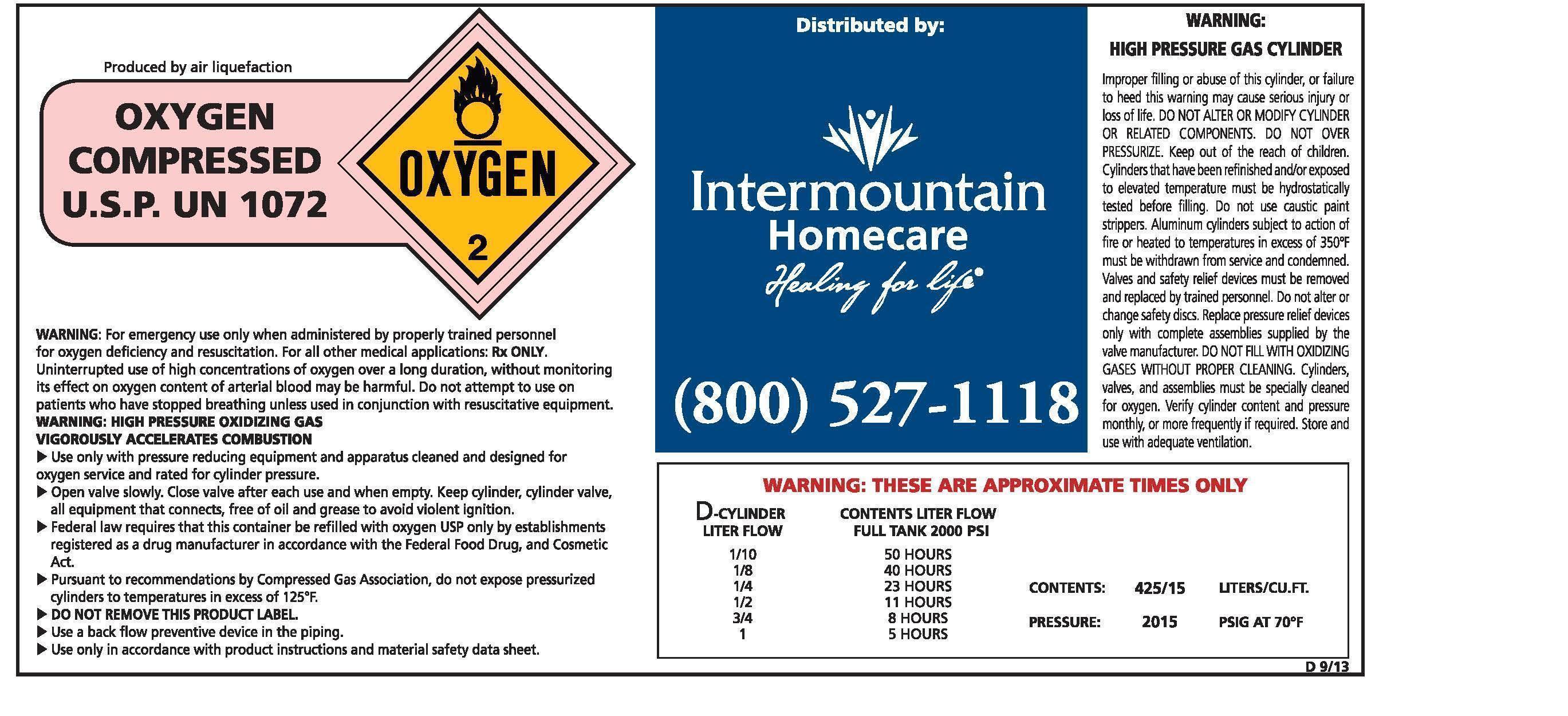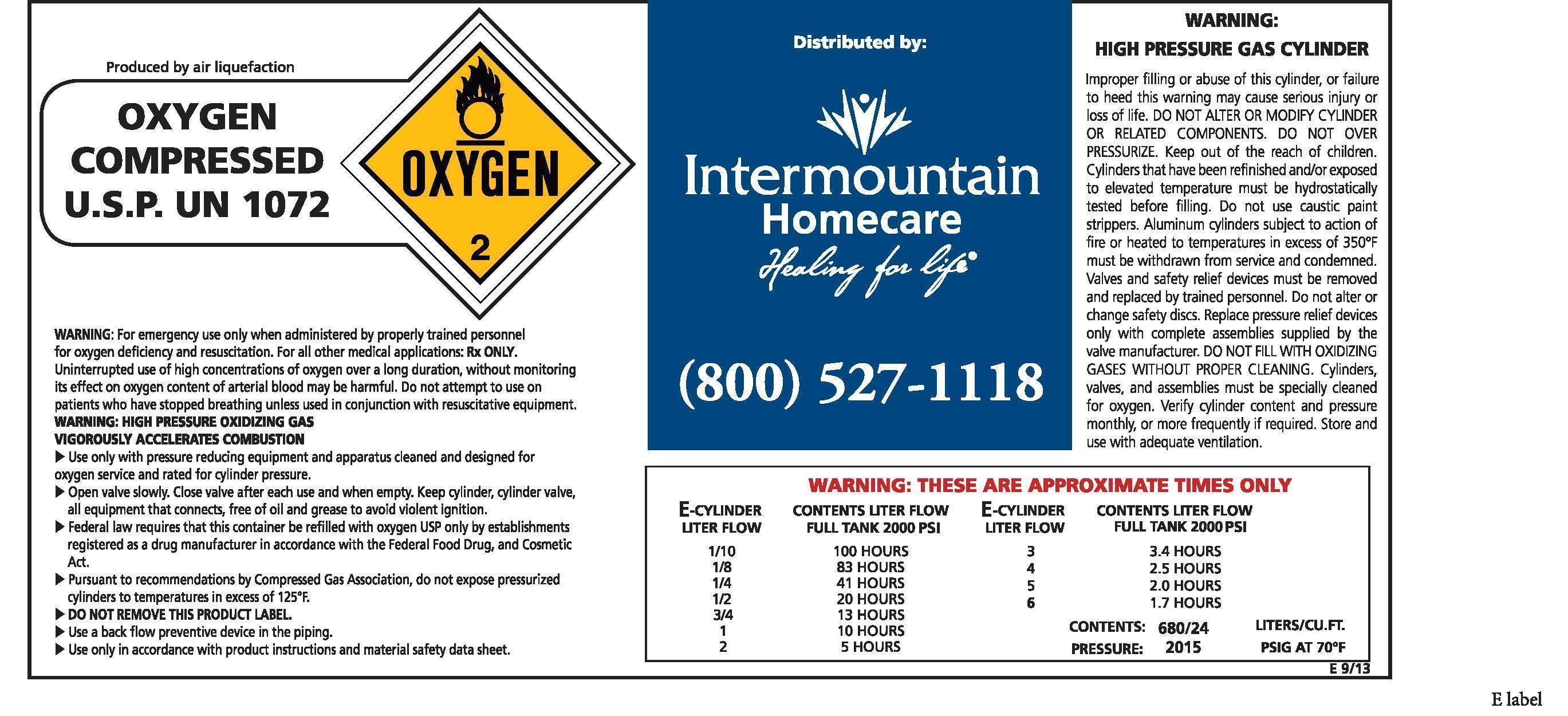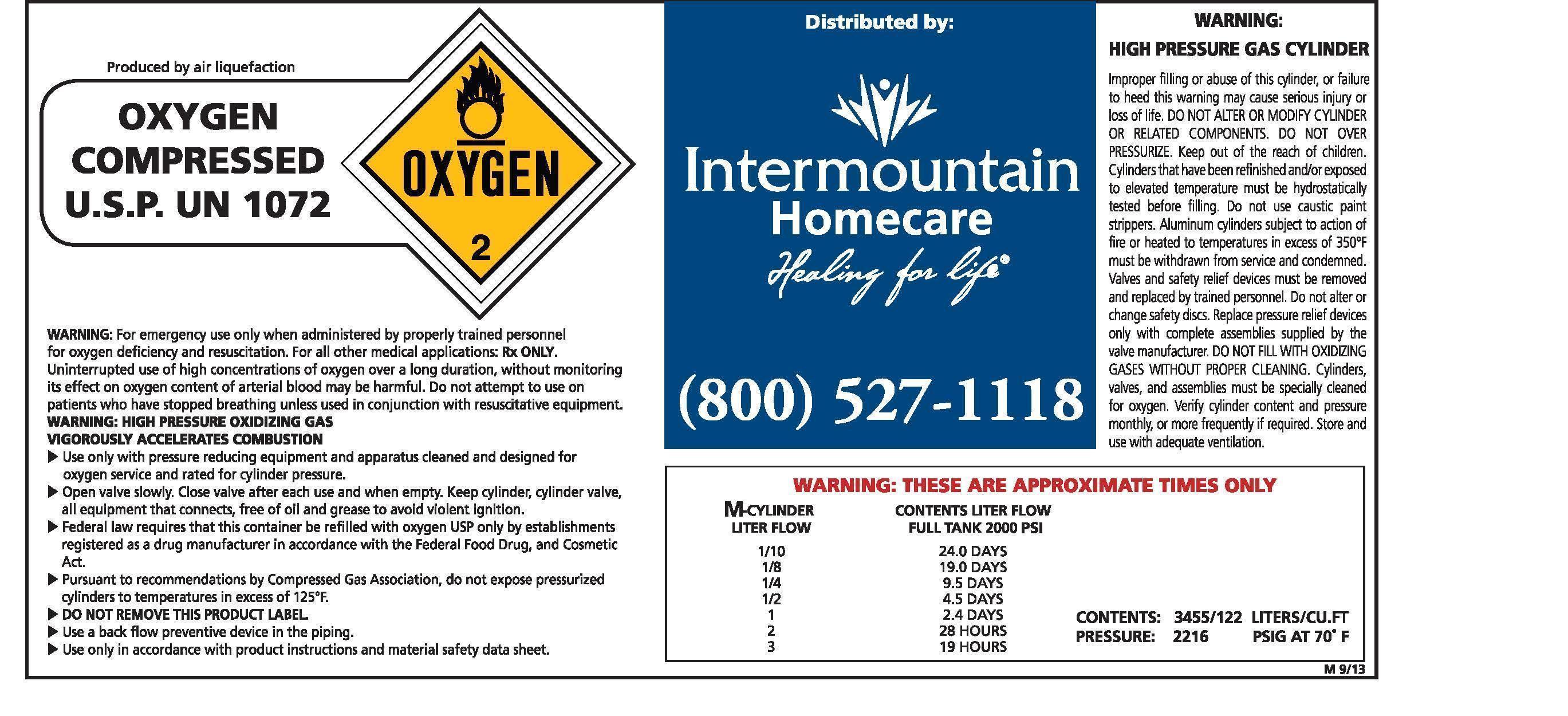 DRUG LABEL: Oxygen
NDC: 62179-1234 | Form: GAS
Manufacturer: Intermountain Home Care
Category: prescription | Type: HUMAN PRESCRIPTION DRUG LABEL
Date: 20251205

ACTIVE INGREDIENTS: OXYGEN 1 L/1 L

Oxygen

OXYGEN COMPRESSED U.S.P. UN 1072

WARNING: For emergency use only when administered by properly trained personnel for oxygen deficiency and resuscitation. For all other medical applications: Rx ONLY. Uninterrupted use of high concentrations of oxygen over a long duration, without monitoring its effect on oxygen content of arterial blood, may be harmful. Do not attempt to use on patients who have stopped breathing unless used in conjunction with resuscitative equipment.

WARNING: HIGH PRESSURE OXIDIZING GAS

VIGOROUSLY ACCELERATES COMBUSTION

Use only with pressure reducing equipment and apparatus cleaned and designed for oxygen service and rated for cylinder pressure.

Open valve slowly. Close valve after each use and when empty. Keep cylinder, cylinder valve, all equipment that connects, free of oil and grease to avoid violent ignition.

Federal law requires that this container be refilled with oxygen USP only by establishments registered as a drug manufacturer in accordance with the Federal Food, Drug, and Cosmetic Act.

Pursuant to recommendations by Compressed Gas Association, do not expose pressurized cylinders to temperatures in excess of 125°F.

DO NOT REMOVE THIS PRODUCT LABEL.

Use a back flow preventive device in the piping.

Use only in accordance with product instructions and material safety data sheet.

WARNING:

HIGH PRESSURE GAS CYLINDER

Improper filling or abuse of this cylinder, or failure to heed this warning may cause serious injury or loss of life. DO NOT ALTER OR MODIFY CYLINDER OR RELATED COMPONENTS. DO NOT OVER PRESSURIZE. Keep out of the reach of children. Cylinders that have been refinished and/or exposed to elevated temperatures must be hydrostatically tested before filling. Do not use caustic paint strippers. Aluminum cylinders subject to action of fire or heated to temperatures in excess of 350°F must be withdrawn from service and condemned. Valves and safety relief devices must be removed and replaced by trained personnel. Do not alter or change safety discs. Replace pressure relief devices only with complete assemblies supplied by the valve manufacturer. DO NOT FILL WITH OXIDIZING GASES WITHOUT PROPER CLEANING. Cylinders, valves, and assemblies must be specially cleaned for oxygen. Verify cylinder content and pressure monthly, or more frequently if required. Store and use with adequate ventilation.